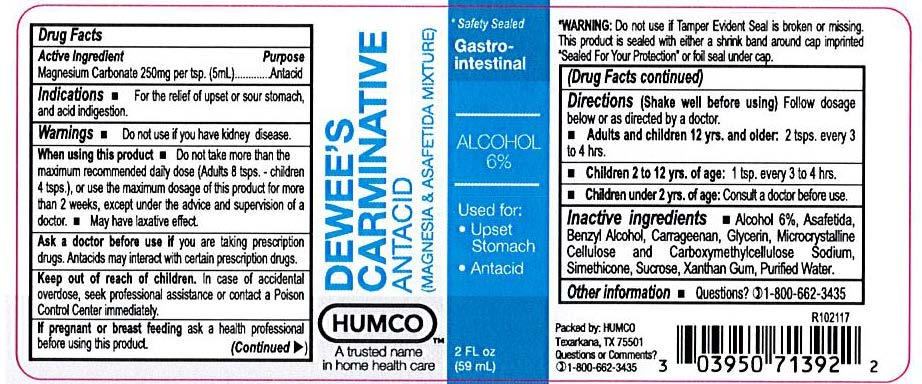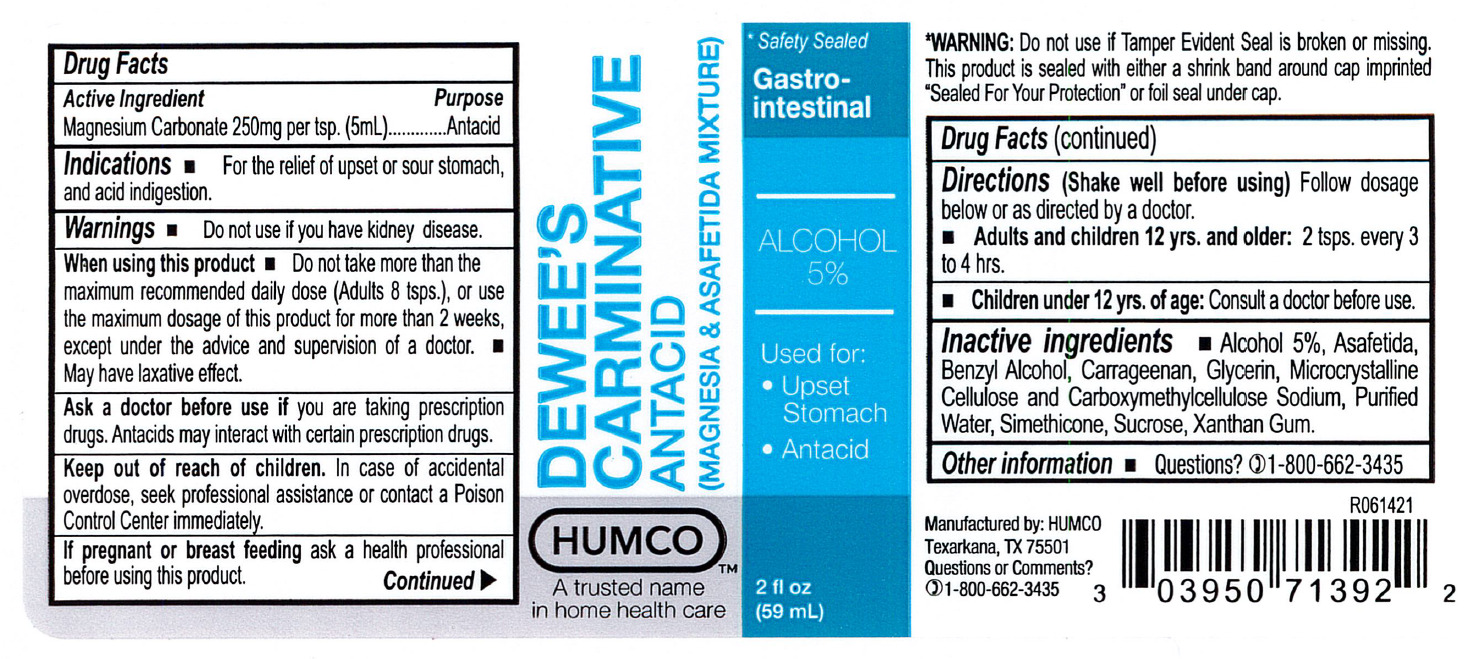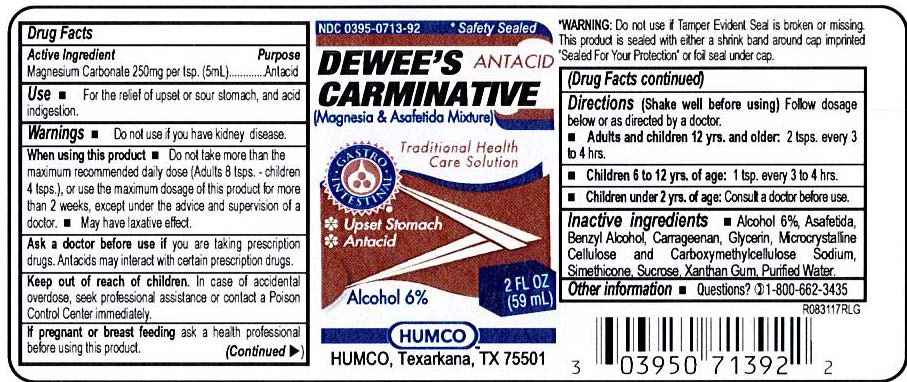 DRUG LABEL: Humco Dewees Carminative
NDC: 0395-0713 | Form: SUSPENSION
Manufacturer: Humco Holding Group, inc.
Category: otc | Type: HUMAN OTC DRUG LABEL
Date: 20231215

ACTIVE INGREDIENTS: MAGNESIUM CARBONATE 50 mg/1 mL
INACTIVE INGREDIENTS: CARRAGEENAN; DIMETHICONOL/TRIMETHYLSILOXYSILICATE CROSSPOLYMER (40/60 W/W; 1000000 PA.S); BENZYL ALCOHOL; CELLULOSE, MICROCRYSTALLINE; ASAFETIDA; GLYCERIN; SUCROSE; WATER; XANTHAN GUM

Humco Dewee's Carminative

Drug Facts

Active Ingredient

Magnesium Carbonate 250 mg per tsp. (5 mL)

Purpose

Carminative

Use

For the temporary relief of upset stomach or sour stomach, and acid indigestion.

Warnings

Do not use if you have kidney desease.

When sing this product

Do not take more than the maximum recommended daily dose (Adults 8 tsps. - children 4 tsps.), or use the maximum dosage of this product for more than 2 weeks, except under the advice and supervision of a doctor.

May have laxative effect.

Ask a doctor before use

If you are taking prescription drugs. Antacids may interact with certain prescription drugs.

Keep out of reach of children.

In the case of accidental overdose, seek professional assistance or contact a Poison Control center immediately.

Directions

(Shake well before using)

Follow dosage below or as directed by a doctor.

Adults and children 12 yrs. and older: 2 tsps. every 3 to 4 hrs.

Children under 12 yrs. of age: consult a doctor before use.

RECENT MAJOR CHANGES

Children under 12 yrs. of age: Consult a doctor befor use. (6/2021)

Inactive ingredients

Alcohol 5%, Asafetida, Avicel, Benzyl Alcohol, Carrageenan, Glycerin, Microcrystalline Cellulose and Carboxymethylcelloulose Sodium, Purified Water, Simethicone, Sucrose, Xanthan Gum

Labels

Old

New Label

New